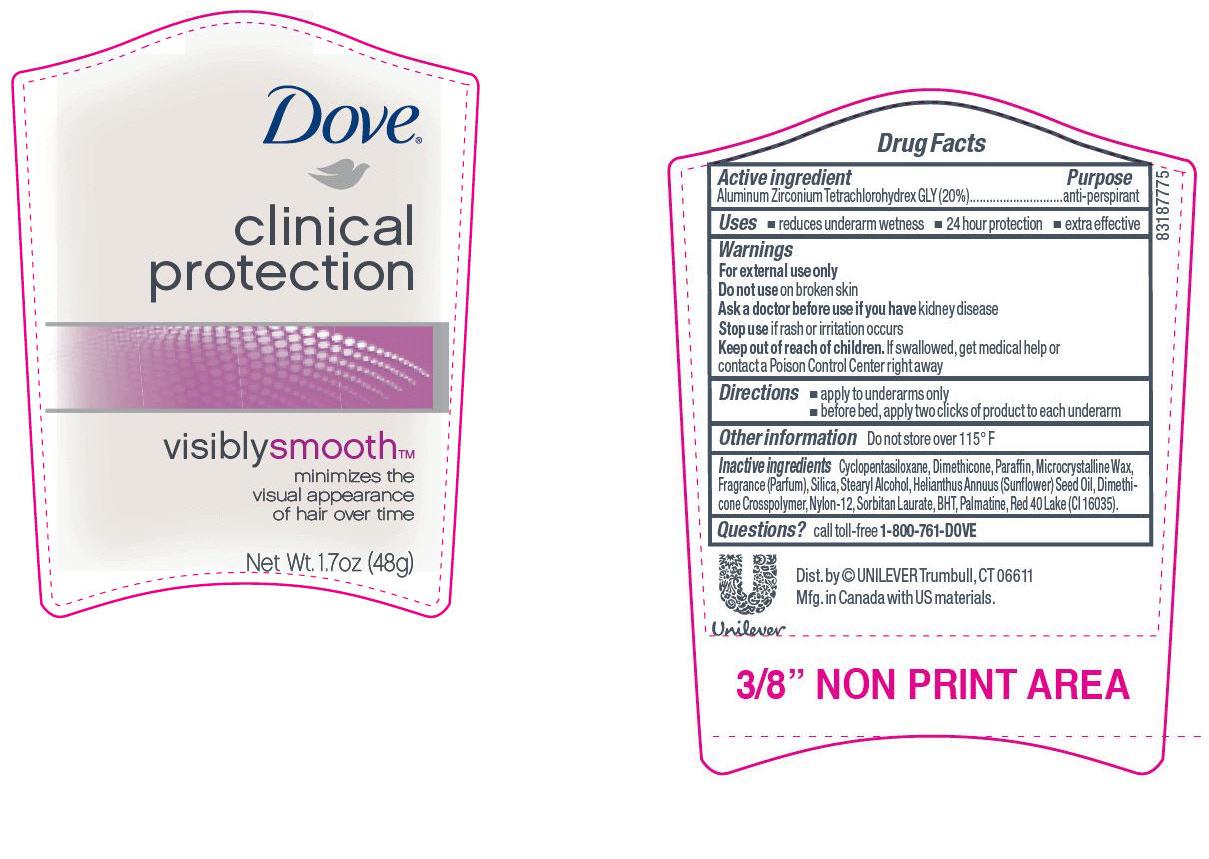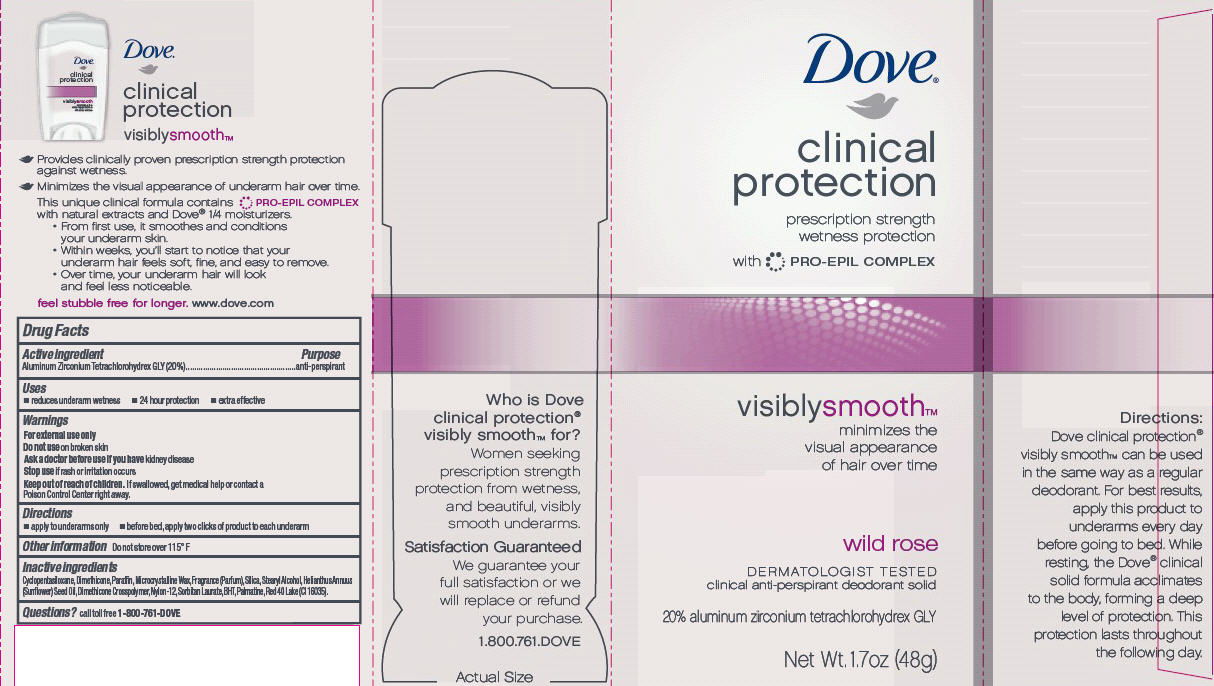 DRUG LABEL: Dove Clinical Protection Visibly Smooth Wild Rose
NDC: 64942-1074 | Form: STICK
Manufacturer: Conopco Inc. d/b/a Unilever
Category: otc | Type: HUMAN OTC DRUG LABEL
Date: 20120131

ACTIVE INGREDIENTS: Aluminum Zirconium Tetrachlorohydrex GLY 20 g/100 g
INACTIVE INGREDIENTS: CYCLOMETHICONE 5; DIMETHICONE; BUTYLATED HYDROXYTOLUENE; PARAFFIN; MICROCRYSTALLINE WAX; SILICON DIOXIDE; SUNFLOWER OIL; PALMATINE; SORBITAN MONOLAURATE

Dove Clinical Protection Visibly Smooth Wild Rose antiperspirant deodorant

Active Ingredient

Aluminum Zirconium Tetrachlorohydrex GLY (20%)

Purpose
anti-perspirant

Uses
· reduces underarm wetness
· 24 hour protection
· extra effective

Warnings
For external use only

Do not use on broken skin

Ask a doctor before use if you have kidney disease

Stop use if rash or irritation occurs

Keep out of reach of children. If swallowed, get medical help or contact a Poison Control Center right away.

Directions
· apply to underarms only
· before bed, apply three clicks of product to each underarm

INACTIVE INGREDIENT

Cyclopentasiloxane, Dimethicone, Paraffin, Microcrystalline Wax, Fragrance (Parfum), Silica, Stearyl Alcohol, Helianthus Annuus (Sunflower) Seed Oil, Dimethicone Crosspolymer, Nylon-12, Sorbitan Laurate, BHT, Palmatine, Red 40 Lake (CI 16035)

Questions? Call toll-free 1-800-761-DOVE

PACKAGE LABEL

1.7 oz PDP

PACKAGE LABEL

1.7 oz carton